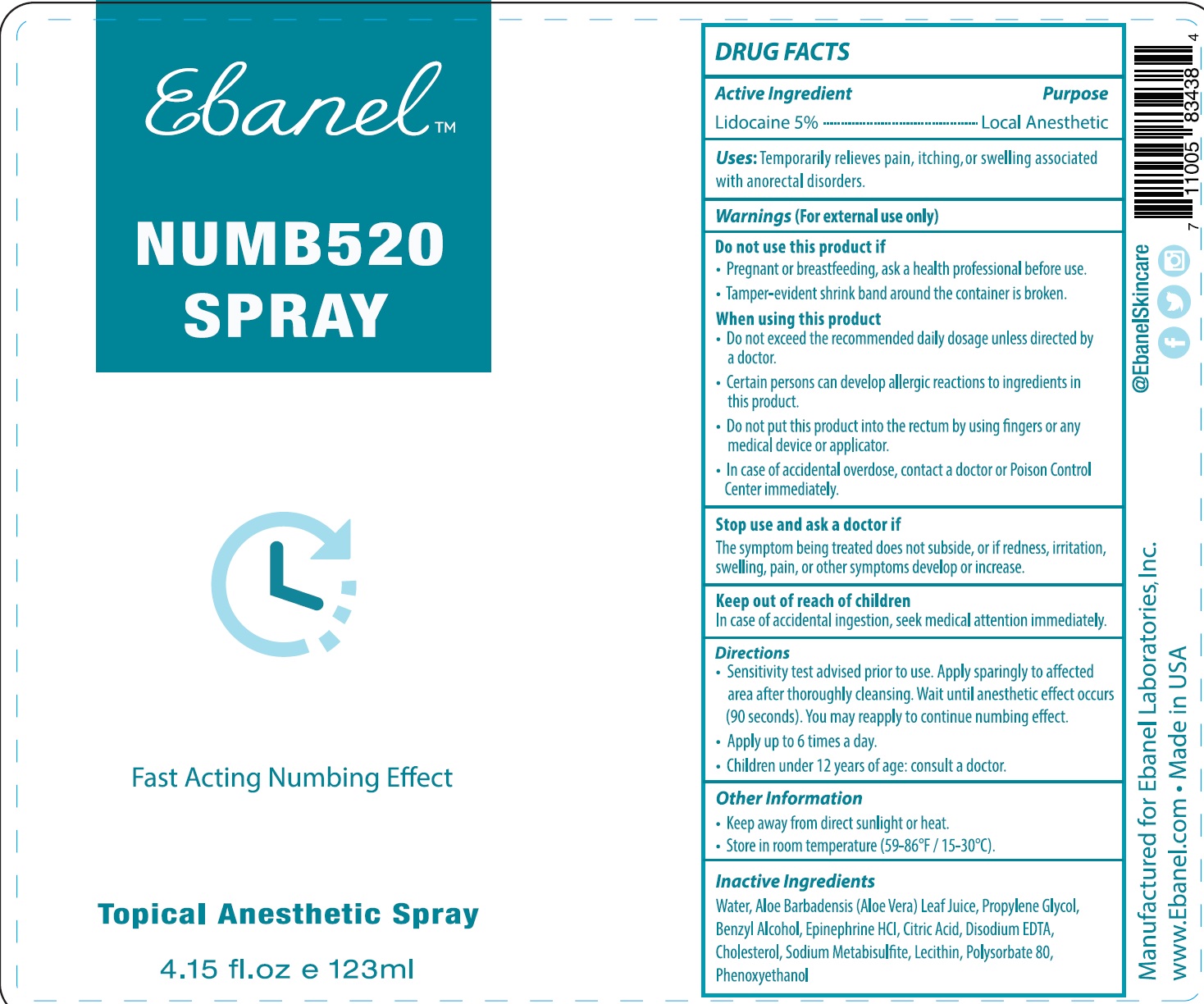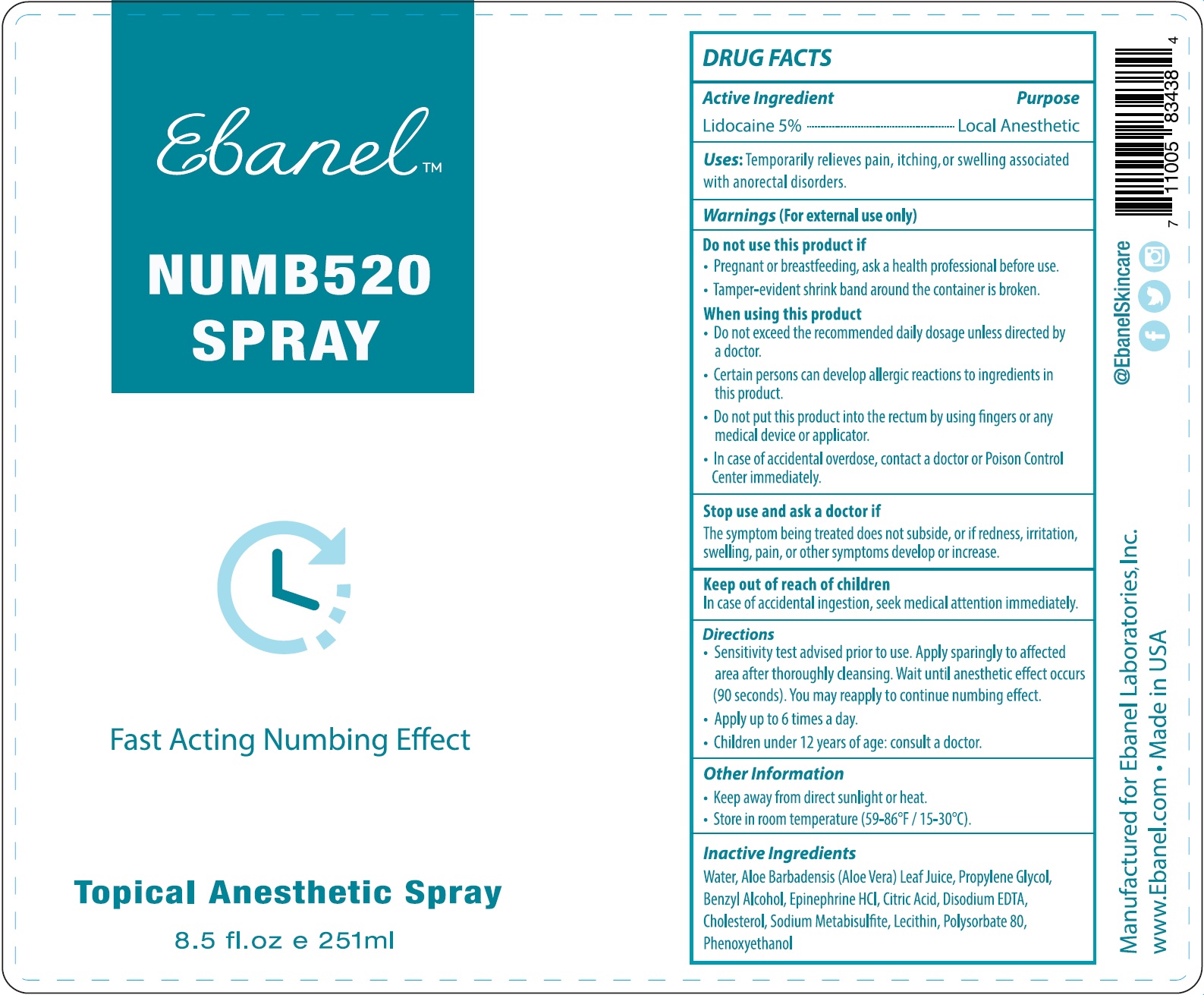 DRUG LABEL: Numb520
NDC: 63742-006 | Form: LIQUID
Manufacturer: Clinical Resolution Laboratory, Inc.
Category: otc | Type: HUMAN OTC DRUG LABEL
Date: 20231226

ACTIVE INGREDIENTS: LIDOCAINE 50 mg/1 mL
INACTIVE INGREDIENTS: CHOLESTEROL; SODIUM METABISULFITE; POLYSORBATE 80; PHENOXYETHANOL; EDETATE DISODIUM ANHYDROUS; WATER; ALOE VERA LEAF; PROPYLENE GLYCOL; BENZYL ALCOHOL; EPINEPHRINE HYDROCHLORIDE; CITRIC ACID MONOHYDRATE

Numb520 Spray

Active Ingredient

Lidocaine 5%

Purpose

Local Anesthetic

Uses:

Temporarily relieves pain, itching, or swelling associated with anorectal disorders.

Warnings

(For external use only)

Do not use this product if

- Pregnant or breastfeeding, ask a health professional before use
- Tamper-evident shrink band around the container is broken.

When using this product

- Do not exceed the recommended daily unless directed by a doctor.
- Certain persons can develop allergic reactions to ingredients in this product.
- Do not put this product into the rectum by using fingers or any medical device or applicator.
- In case of accidental overdose, contact a doctor or Poison Control Center immediately.

Stop use and ask a doctor if

The symptom being treated does not subside, or if redness, irritation, swelling, pain, or other symptoms develop or increase.

Keep out of reach of children

In case of accidental ingestion, seek medical attention immediately.

Directions

- Sensitivity test advised prior to use. Apply sparingly to affected area after thoroughly cleansing. Wait until anesthetic effect occurs (90 seconds). You may reapply to continue numbing effect.
- Apply up to 6 times a day.
- Children under 12 year of age: consult a doctor.

Other Information

- Keep away from direct sunlight or heat.
- Store in room temperature (59-86°F / 15-30°C).

Inactive Ingredients

Water, Aloe Barbadensis (Aloe Vera) Leaf Juice, Propylene Glycol, Benzyl Alcohol, Epinephrine HCL, Citric Acid, Disodium EDTA, Cholesterol, Sodium Metabisulfite, Lecithin, Polysorbate 80, Phenoxyethanol